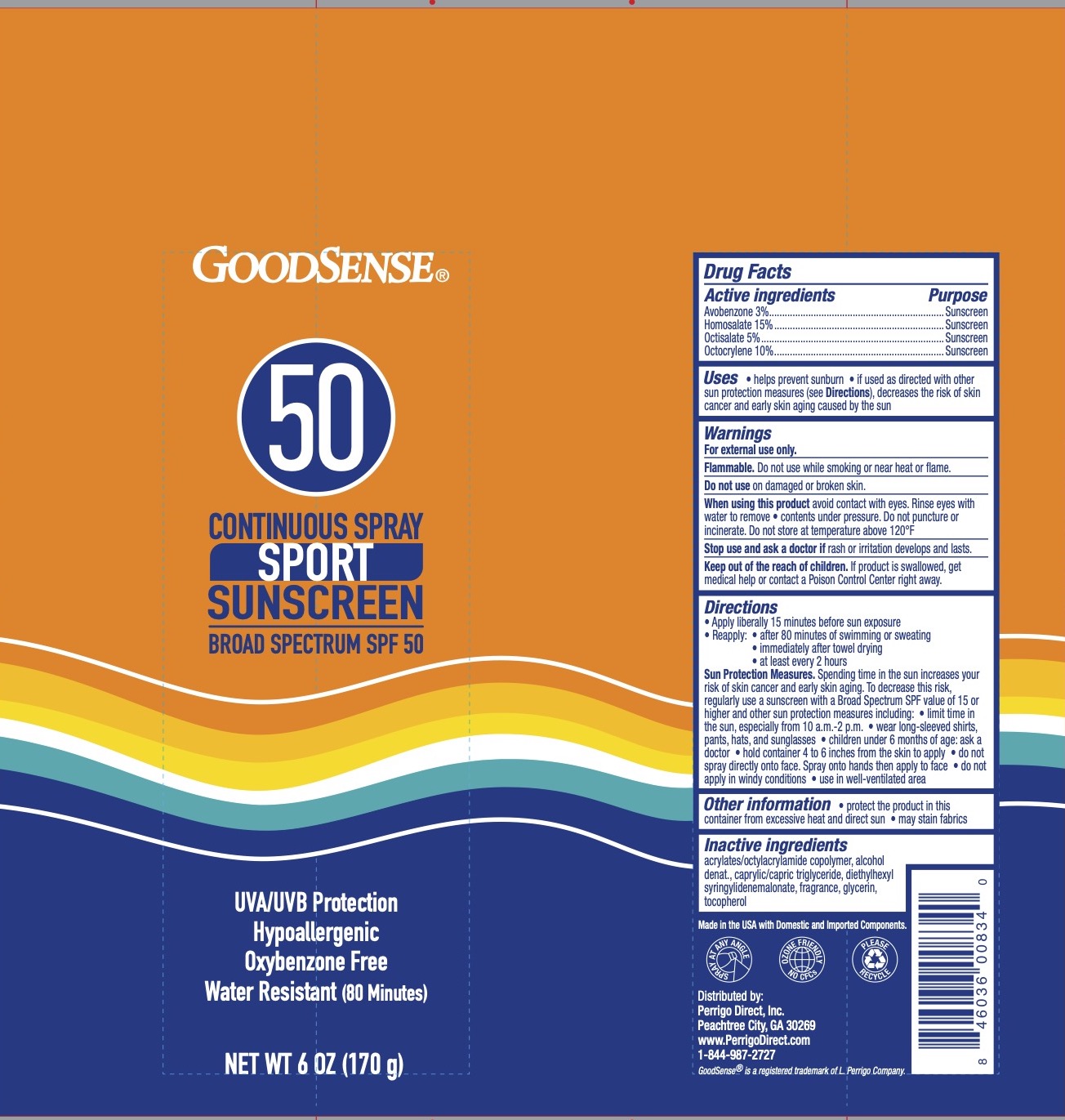 DRUG LABEL: SPF 50 Sport Sunscreen
NDC: 50804-787 | Form: SPRAY
Manufacturer: Geiss, Destin, & Dunn, Inc
Category: otc | Type: HUMAN OTC DRUG LABEL
Date: 20251121

ACTIVE INGREDIENTS: OCTISALATE 5 g/100 g; AVOBENZONE 3 g/100 g; HOMOSALATE 15 g/100 g; OCTOCRYLENE 10 g/100 g
INACTIVE INGREDIENTS: ALCOHOL; GLYCERIN; ACRYLATE/ISOBUTYL METHACRYLATE/N-TERT-OCTYLACRYLAMIDE COPOLYMER (75000 MW); CAPRYLYL TRISILOXANE; MEDIUM-CHAIN TRIGLYCERIDES; DIETHYLHEXYL SYRINGYLIDENEMALONATE; STEAROXYTRIMETHYLSILANE; TOCOPHEROL

Active Ingredients

Avobenzone 3%, Homosalate 15%, Octisalate 5%, Octocrylene 10%

Purpose

Sunscreen

Uses

- Helps prevent sunburn

Warnings

For external use only. Flammable: do not use while smoking or near heat or flame.

Do not use on damaged or broken skin. When using this product keep out of eyes. Rinse eyes with water to remove. Contents under pressure. Do not puncture or incinerate. Do not store at temperature above 120 degrees F.

Stop use and ask a doctor if rash occurs.

Keep Out of Reach of Children.

If swallowed, get medical help or contact a Poison Control Center right away.

Directions

Apply liberally 15 minutes before sun exposure. Reapply:

- after 80 minutes of swimming or sweating
- immediately after towel drying
- at least every 2 hours

Sun protection measures: spending time n the sun increases your risk of skin cancer and early skin aging. To decrease risk, regularly use a sunscreen with broad spectrum SPF of 15 or higher and other sun protection measure including:

- limit time in the sun, especially from 10 am to 2 pm
- wear long-sleeved shirts, pants, hats, and sunglasses.
- Children under 6 months: ask a doctor.

Hold container 4 to 6 inches from the skin to apply. Do not spray directly into face. Spray on hands then apply to face. Do no apply in windy conditions. Use in a well-ventilated area.

Inactive Ingredients

Acrylates/Octylacrylamide Copolymer, Alcohol Denat., Caprylic/Capric Triglyceride, Diethylhexyl Syringylidenemalonate, Fragrance, Glycerin, Stearoxytrimethysilane, Tocopherol.